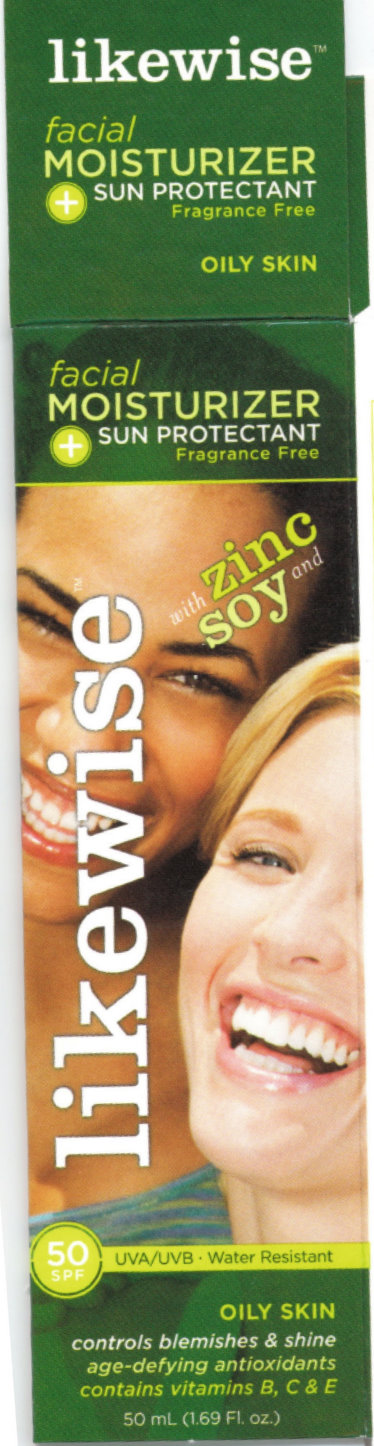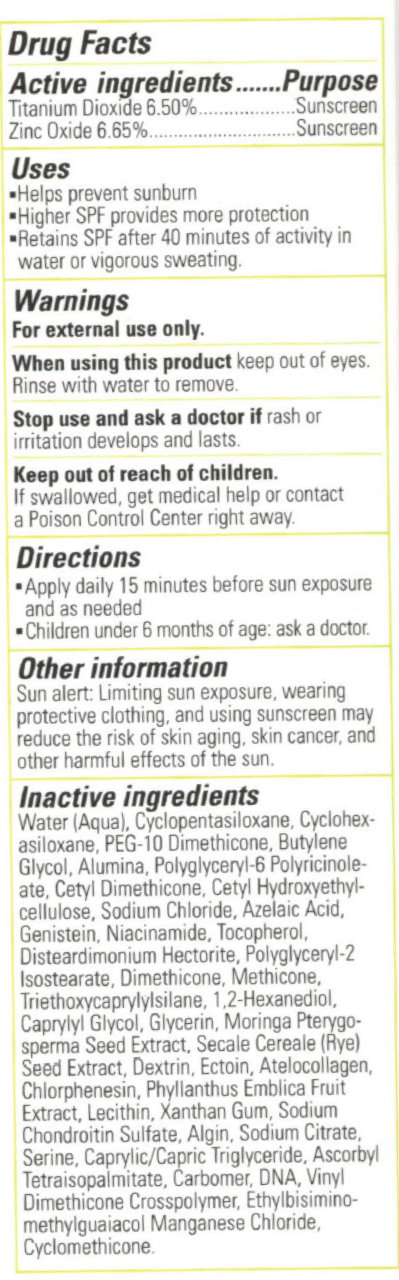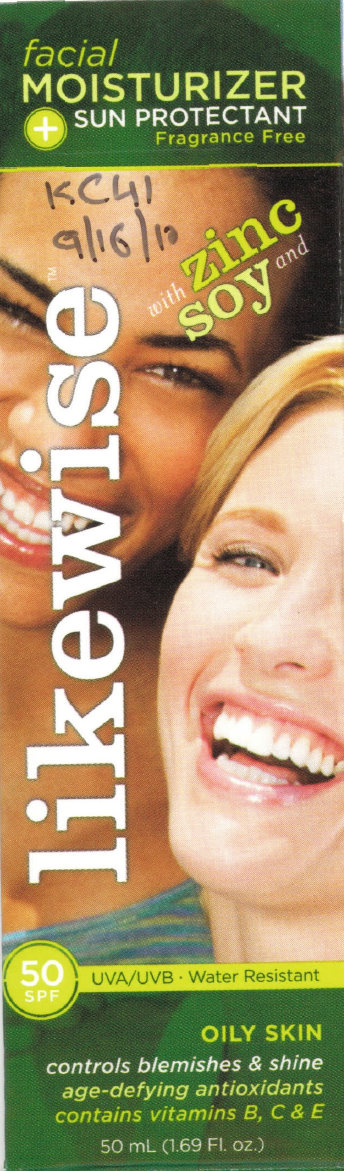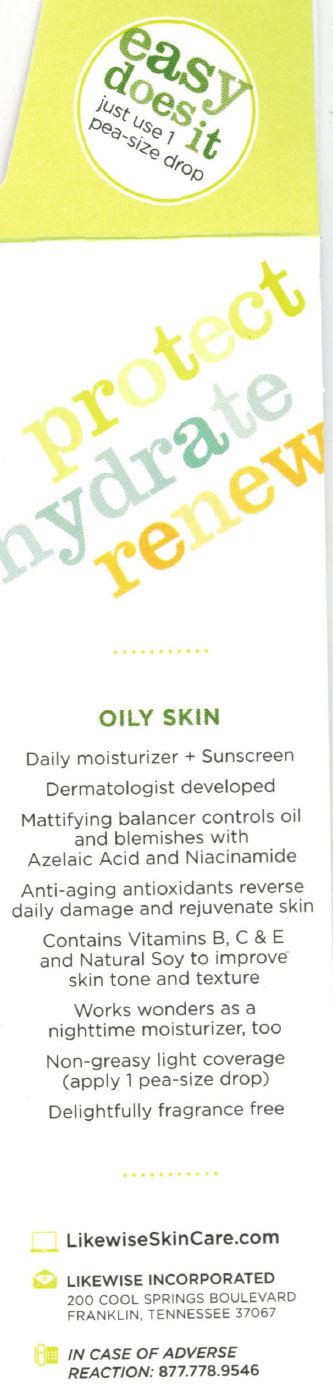 DRUG LABEL: Likewise Facial Moisturizer - Sun Protectant SPF 50 Oily Skin
NDC: 76229-234 | Form: CREAM
Manufacturer: Likewise Incorporated
Category: otc | Type: HUMAN OTC DRUG LABEL
Date: 20231212

ACTIVE INGREDIENTS: TITANIUM DIOXIDE 65 mg/1 mL; ZINC OXIDE 66.5 mg/1 mL
INACTIVE INGREDIENTS: WATER; CYCLOMETHICONE 5; CYCLOMETHICONE 6; BUTYLENE GLYCOL; ALUMINUM OXIDE; SODIUM CHLORIDE; AZELAIC ACID; GENISTEIN; NIACINAMIDE; TOCOPHEROL; DIMETHICONE; TRIETHOXYCAPRYLYLSILANE; 1,2-HEXANEDIOL; CAPRYLYL GLYCOL; GLYCERIN; MORINGA OLEIFERA SEED; RYE; ICODEXTRIN; ECTOINE; CHLORPHENESIN; PHYLLANTHUS EMBLICA FRUIT; XANTHAN GUM; SODIUM CHONDROITIN SULFATE (PORCINE; 5500 MW); SODIUM ALGINATE; SODIUM CITRATE; SERINE; MEDIUM-CHAIN TRIGLYCERIDES; HERRING SPERM DNA; CYCLOMETHICONE

Likewise Facial Moisturizer - Sun Protectant SPF 50 Oily Skin

ACTIVE INGREDIENT

Active Ingredients..............................Purpose Titanium Dioxide 6.50%...................Sunscreen Zinc Oxide 6.65%............................Sunscreen

PURPOSE

Uses - Helps prevent sunburn - Higher SPF provides more protection - Retains SPF after 40 minutes of activity in water or vigorous sweating.

Uses

- Helps prevent sunburn
- Higher SPF provides more protection
- Retains SPF after 40 minutes of activity in water or vigorous sweating.

Warnings For external use only

When using this product keep out of eyes. Rinse with water to remove.

Stop use and ask a doctor if rash or irritation develops and lasts.

Keep out of reach of children.

If swallowed, get medical help or contact a Poison Control Center right away.

OTHER SAFETY INFORMATION

If swallowed, get medical help or contact a Poison Control Center right away.

DOSAGE AND ADMINISTRATION

Directions - Apply daily 15 minutes before sun exposure and as needed - Children under 6 months of age: ask a doctor.

Other information Sun alert: Limiting sun exposure, wearing protective clothing, and using sunscreen may reduce the risk of skin aging, skin cancer, and other harmful effects of the sun.

INACTIVE INGREDIENT

Inactive ingredients Water (Aqua), Cyclopentasiloxane, Cyclohexasiloxane, PEG-10 Dimethicone, Butylene Glycol, Alumina, Polyglyceryl-6 Polyricinoleate, Cetyl Dimethicone, Cetyl Hydroxyethylcellulose, Sodium Chloride, Azelaic Acid, Genistein, Niacinamide, Tocopherol, Disteardimonium Hectorite, Polyglyceryl-2 Isostearate, Dimethicone, Methicone, Triethoxycaprylylsilane, 1,2-Hexanediol, Caprylyl Glycol, Glycerin, Moringa Pterygosperma Seed Extract, Secale Cereale (Rye) Seed Extract, Dextrin, Ectoin, Atelocollagen, Chlorphenesin, Phyllanthus Emblica Fruit Extract, Lecithin, Xanthan Gum, Sodium Chondroitin Sulfate, Algin, Sodium Citrate, Serine, Caprylic/Capric Triglyceride, Ascorbyl Tetraisopalmitate, Carbomer, DNA, Vinyl Dimethicone Crosspolymer, Ethylbisiminomethylguaiacol Manganese Chloride, Cyclomethicone.

DESCRIPTION

OILY SKIN Daily moisturizer + Sunscreen Dermatologist developed Mattifying balancer controls oil and blemishes with Azelaic Acid and Niacinamide Anti-aging antioxidants reverse daily damage and rejuvenate skin Contains Vitamins B, C and E and Natural Soy to improve skin tone and texture Works wonders as a nightime moisturizer, too Non-greasy light coverage (apply 1 pea-size dop) Delightfully fragrance free LikewiseSkinCare.com LIKEWISE INCORPORATED 200 COOL SPRINGS BOULEVARD FRANKLIN, TENNESSEE 37067 IN CASE OF ADVERSE REACTION: 877.778.9546

PACKAGE LABEL

likewise facial MOISTURIZER + SUN PROTECTANT Fragrance Free OILY SKIN facial MOISTURIZER + SUN PROTECTANT Fragrance Free likewise with Zinc soy and 50 SPF UVA/UVB - Water Resistant OILY SKIN controls blemishes and shine age-defying antioxidants contains vitamins B, C and E 50 mL (1.69 Fl.oz.)

Drug Facts

PACKAGE LABEL

easy does it just use 1 pea-size drop protect hydrate renew LikewiseSkinCare.com LIKEWISE INCORPORATED 200 COOL SPRINGS BOULEVARD FRANKLIN, TENNESSEE 37067 IN CASE OF ADVERSE REACTION: 877.778.9546